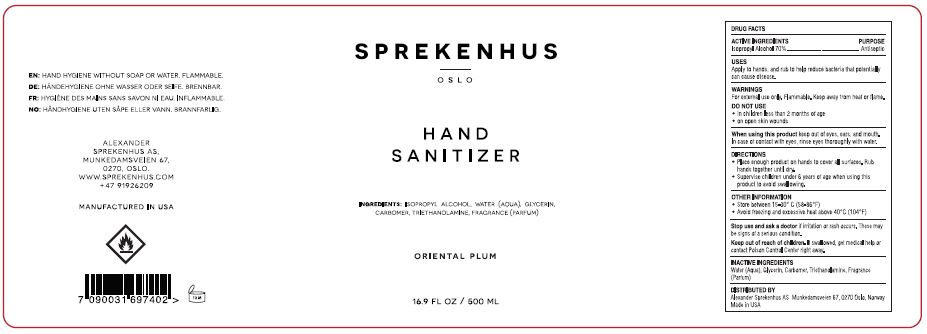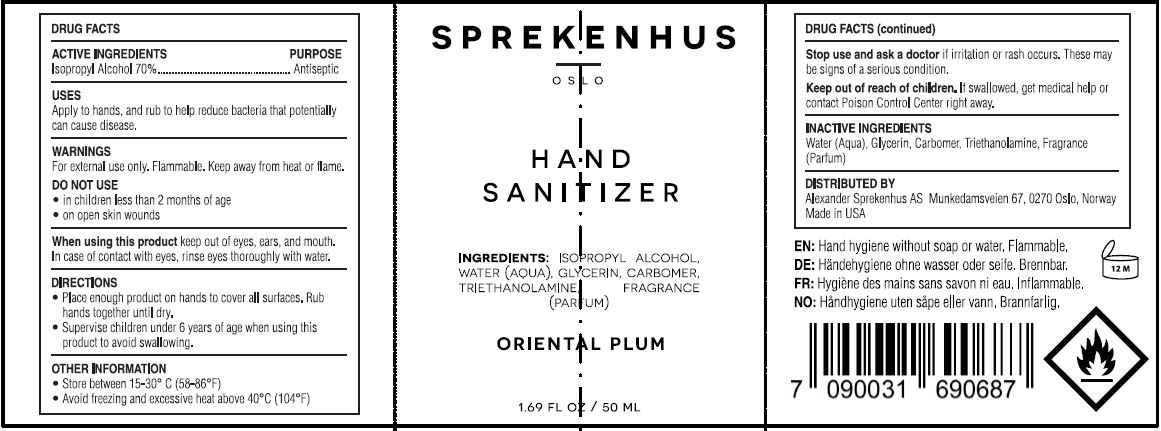 DRUG LABEL: HAND SANITIZER
NDC: 80574-101 | Form: GEL
Manufacturer: Alexander Sprekenhus AS
Category: otc | Type: HUMAN OTC DRUG LABEL
Date: 20210429

ACTIVE INGREDIENTS: ISOPROPYL ALCOHOL 70 mL/100 mL
INACTIVE INGREDIENTS: WATER; GLYCERIN; CARBOMER HOMOPOLYMER, UNSPECIFIED TYPE; TROLAMINE

ALEXANDER SPREKENHAUS - HAND SANITIZER GEL - 70% ISOPROPYL ALCOHOL

ACTIVE INGREDIENT

ISOPROPYL ALCOHOL 70%

PURPOSE

ANTISEPTIC

USES

Apply to hands, and rub to help reduce bacteria that potentially can cause disease.

WARNING

For external use only. Flammable, Keep away from heat or flame.

DO NOT USE

- in children less than 2 months of age
- on open skin wounds

When using this product keep out of eyes, ears, and mouth. In case of contact with eyes, rinse eyes thoroughly with water.

KEEP OUT OF REACH OF CHILDREN.

DIRECTIONS

- Place enough product on hands to cover all surtaces. Rub hands together until dry.
- Supervise children under 6 years of age when using this product to avoid swallowing.

OTHER INFORMATION

- Store between 15-30° C {58-86° F)
- Avoid freezing and excessive heat above 40° C (104° F)

INACTIVE INGREDIENTS

WATER (AQUA), CARBOMER, GLYCERIN, TRIETHANOLAMINE, FRAGRANCE (PARFUM)